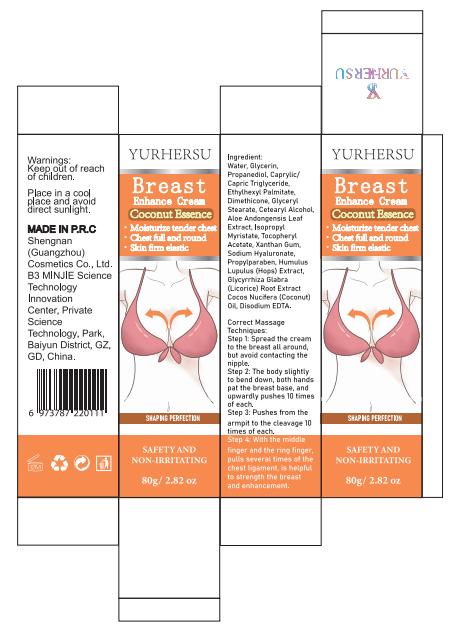 DRUG LABEL: BreastEnhanceCream
NDC: 84019-012 | Form: CREAM
Manufacturer: Shengnan (Guangzhou) Cosmetics Co., LTD
Category: otc | Type: HUMAN OTC DRUG LABEL
Date: 20241127

ACTIVE INGREDIENTS: XANTHAN GUM 100 mg/1 g
INACTIVE INGREDIENTS: GLYCERIN; ETHYLHEXYL PALMITATE; PROPANEDIOL; WATER; CAPRYLIC/CAPRIC TRIGLYCERIDE

BreastEnhanceCream

Keep out of reach of children

PURPOSE

Breast Enhance

Stop use and ask doctor if rash occurs.

ACTIVE INGREDIENT

Xanthan Gum

WHEN USING

Do not apply to wounds or damaged skin.

INACTIVE INGREDIENT

Water
Glycerin
Propanediol
Caprylic/Capric Triglyceride
Ethylhexyl Palmitate
Dimethicone
Glyceryl Stearate
Cetearyl Alcohol
Aloe Andongensis Leaf Extract
Isopropyl Myristate
Tocopheryl Acetate
Sodium Hyaluronate
Propylparaben
Humulus Lupulus (Hops) Extract
Glycyrrhiza Glabra (Licorice) Root Extract
Cocos Nucifera (Coconut) Oil
Disodium EDTA

DOSAGE AND ADMINISTRATION

Apply 1-2 times a day

INDICATIONS AND USAGE

Step 1:Spread the creamto the breast all around,but avoid contacting thenipple.Step 2: The body slightlyto bend down, both handspat the breast base, andupwardly pushes 10 timesof each.Step 3: Pushes from thearmpit to the cleavage 10times of each.Step 4: With the middlefinger and the ring finger,pulls several times of thechest ligament, is helpfulto strength the breastand enhancement.

KEEP OUT OF REACH OF CHILDREN SECTION